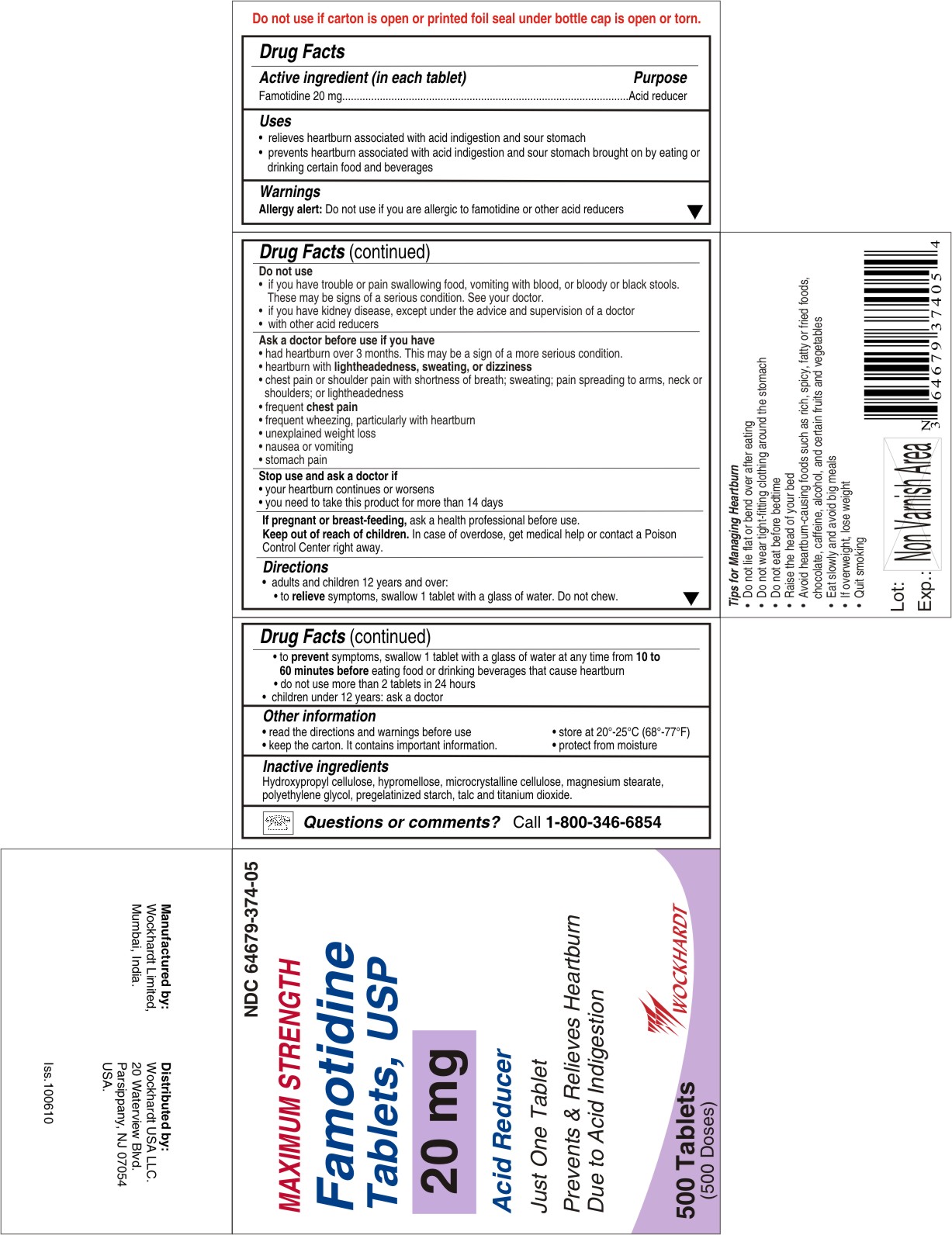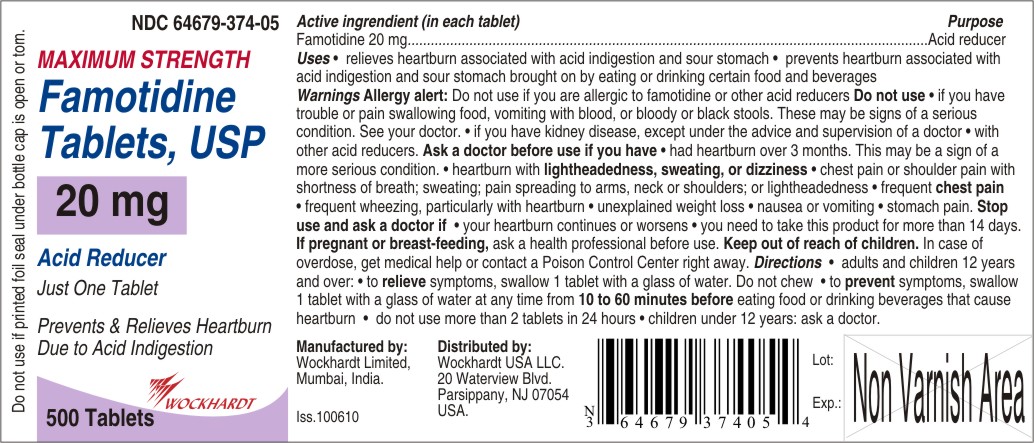 DRUG LABEL: FAMOTIDINE
NDC: 55648-374 | Form: TABLET
Manufacturer: WOCKHARDT LIMITED
Category: otc | Type: HUMAN OTC DRUG LABEL
Date: 20120807

ACTIVE INGREDIENTS: FAMOTIDINE 20 mg/1 1
INACTIVE INGREDIENTS: CELLULOSE, MICROCRYSTALLINE; STARCH, CORN; HYDROXYPROPYL CELLULOSE, LOW SUBSTITUTED; TALC; MAGNESIUM STEARATE; HYPROMELLOSE 2910 (6 MPA.S); TITANIUM DIOXIDE; POLYETHYLENE GLYCOL 400

Famotidine Tablets, USP
20 mg

Drugs Facts

Active ingredient (in each tablets)

Famotidine USP 20 mg

Purpose

Acid reducer

Uses

- relieves heartburn associated with acid indigestion and sour stomach
- prevents heartburn associated with acid indigestion and sour stomach brought on by eating or drinking certain food and beverages

Warnings

Allergy alert: Do not use if you are allergic to famotidine or other acid reducers

Do not use

- if you have trouble or pain swallowing food, vomiting with blood, or bloody or black stools. These may be signs of a serious condition. See your doctor.
- if you have kidney disease, except under the advice and supervision of a doctor
- with other acid reducers

Ask a doctor before use if you have

- had heartburn over 3 months. This may be a sign of a more serious condition.
- heartburn with lightheadedness, sweating, or dizziness
- chest pain or shoulder pain with shortness of breath; sweating; pain spreading to arms, neck or shoulders; or lightheadedness
- frequent chest pain
- frequent wheezing, particularly with heartburn
- unexplained weight loss
- nausea or vomiting
- stomach pain

Stop use and ask a doctor if

- your heartburn continues or worsens
- you need to take this product for more than 14 days

PREGNANCY OR BREAST FEEDING

If pregnant or breast-feeding, ask a health professional before use.

Keep out of reach of children. In case of overdose, get medical help or contact a Poison Control Center right away.

Directions

- adults and children 12 years and over:
- to relieve symptoms, swallow 1 tablet with a glass of water. Do not chew.
- to prevent symptoms, swallow 1 tablet with a glass of water at any time from 10 to 60 minutes before eating food or drinking beverages that cause heartburn
- do not use more than 2 tablets in 24 hours
- children under 12 years: ask a doctor

Other information

- read the directions and warnings before use
- store at 20°-25°C (68°-77°F)
- keep the carton. It contains important information.
- protect from moisture

Inactive ingredients

Hydroxypropyl cellulose, hypromellose, microcrystalline cellulose, magnesium stearate, polyethylene glycol, pregelatinized starch, talc and titanium dioxide.

Questions or comments?

Call 1-800-346-6854
Manufactured by:
Wockhardt Limited,
Mumbai, India.
Distributed by:
Wockhardt USA LLC.
20 Waterview Blvd.
Parsippany, NJ 07054
USA.
Iss.130810